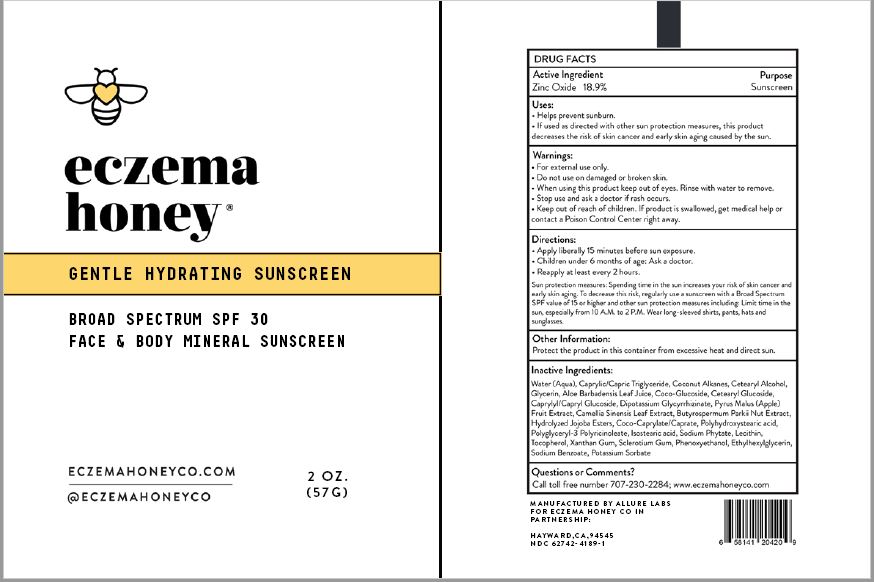 DRUG LABEL: Gentle Hydrating Sunscreen Broad Spectrum SPF 30
NDC: 62742-4189 | Form: CREAM
Manufacturer: Allure Labs Inc
Category: otc | Type: HUMAN OTC DRUG LABEL
Date: 20200824

ACTIVE INGREDIENTS: ZINC OXIDE 189 mg/1 g
INACTIVE INGREDIENTS: WATER; MEDIUM-CHAIN TRIGLYCERIDES; COCONUT ALKANES; CETOSTEARYL ALCOHOL; GLYCERIN; ALOE VERA LEAF; COCO GLUCOSIDE; CETEARYL GLUCOSIDE; CAPRYLYL/CAPRYL OLIGOGLUCOSIDE; APPLE; GREEN TEA LEAF; SHEANUT; HYDROLYZED JOJOBA ESTERS (ACID FORM); COCO-CAPRYLATE/CAPRATE; GLYCYRRHIZINATE DIPOTASSIUM; POLYHYDROXYSTEARIC ACID (2300 MW); POLYGLYCERYL-3 RICINOLEATE; ISOSTEARIC ACID; LECITHIN, SOYBEAN; HEXASODIUM PHYTATE; ETHYLHEXYLGLYCERIN; XANTHAN GUM; TOCOPHEROL; BETASIZOFIRAN; PHENOXYETHANOL; SODIUM BENZOATE; POTASSIUM SORBATE

DRUG FACTS

Active Ingredients:

Zinc Oxide 18.9%

Purpose: Sunscreen

Uses:

- Helps prevent sunburn.
- If used as directed with other sun protection measures (see Direction), this product decreases the risk of skin cancer and early skin aging caused by the sun.

WARNINGS AND PRECAUTIONS

Warning: For external use only.

Do not use: on damaged or broken skin.

When using this product: Keep out of eyes. Rinse with water to remove.

Stop use and ask a doctor: If rash occurs.

Keep out of reach of children: If product is swallowed, get medical help or contact a Poison Control Center right away.

Directions:

- Apply generously 15 minutes before sun exposure.
- Children under 6 months of age: Ask a doctor.
- Reapply at least every 2 hours.
- Sun protection measures: Spending time in the sun increase your risk of skin cancer and early skin aging. To decrease this risk, regularly use a sunscreen with a Broad Spectrum SPF value of 15 or higher and other sun protection measures including:
- Limit time in the sun, especially from 10am - 2pm.
- Wear long sleeved shirts, pants, hats and sunglasses.

Other Information: Protect the product from excessive heat and direct sun.

INACTIVE INGREDIENT

Inactive Ingredients: Water (Aqua), Caprylic/Capric Triglyceride, Coconut Alkanes, Cetearyl Alcohol, Glycerin, Aloe Barbadensis Leaf Juice, Pyrus Malus (Apple) Fruit Extract, Coco-Glucoside, Cetearyl Glucoside, Caprylyl/Capryl Glucoside, Dipotassium Glycyrrhizate, Camellia Sinensis Leaf Extract, Butyrospermum Parkii Nut Extract, Hydrolyzed Jojoba Esters, Coco-Caprylate/Caprate, Polyhydroxystearic Acid, Polyglyceryl-3 Polyricinoleate, Isostearic Acid, Sodium Phytate, Lecithin, Tocopherol, Xanthan Gum, Sclerotium Gum, Phenoxyethanol, Ethylhexylglycerin, Sodium Benzoate, Potassium Sorbate.

Questions or Comments?

Call toll free 707-230-2284; www.eczemahoneyco.com

PACKAGE LABEL

Manufactured by Allure Labs

For Eczema Honey CO IN

Partnership:

Hayward, CA, 94545